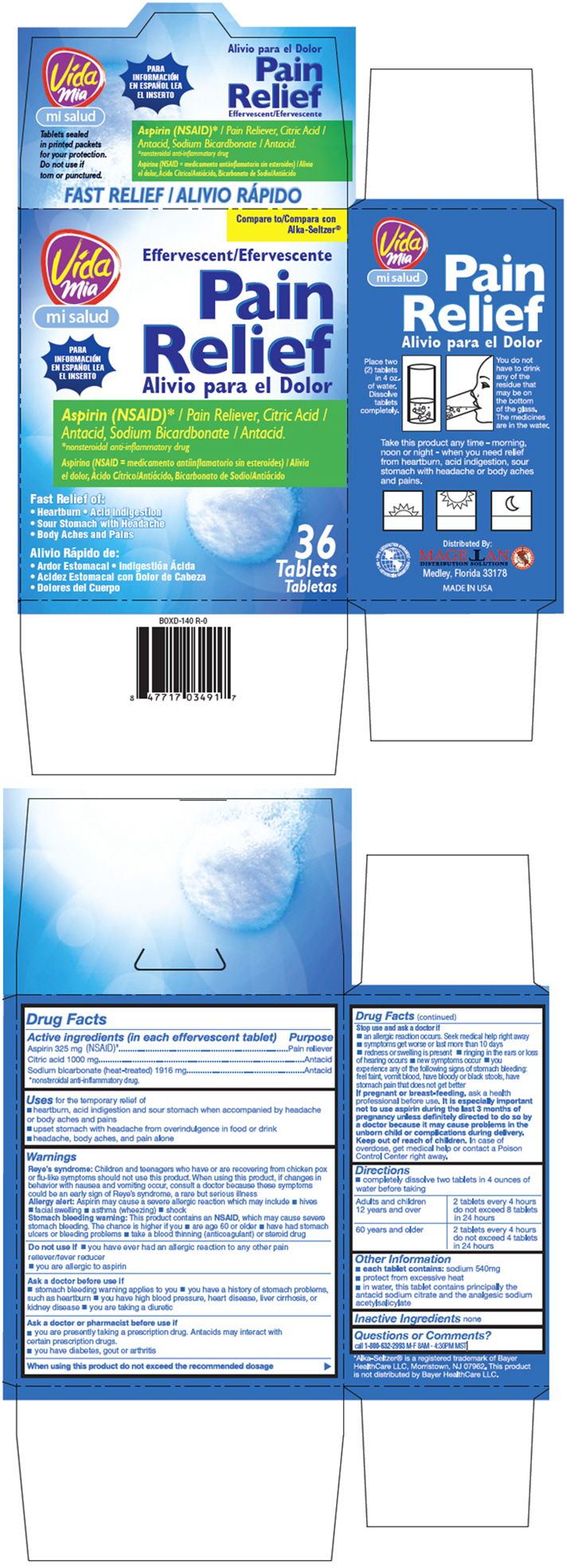 DRUG LABEL: Vida Mia Pain Relief
NDC: 59970-205 | Form: TABLET, EFFERVESCENT
Manufacturer: Navarro Discount Pharmacies, LLC
Category: otc | Type: HUMAN OTC DRUG LABEL
Date: 20140910

ACTIVE INGREDIENTS: Aspirin 325 mg/1 1; Citric Acid Monohydrate 1000 mg/1 1; Sodium Bicarbonate 1916 mg/1 1

Vida Mia Pain Relief

Drug Facts

ACTIVE INGREDIENT

Active ingredients (in each effervescent tablet) | Purpose
Aspirin 325 mg (NSAID) [nonsteroidal anti-inflammatory drug.] | Pain reliever
Citric acid 1000 mg | Antacid
Sodium bicarbonate (heat-treated) 1916 mg | Antacid

Uses

for the temporary relief of

- heartburn, acid indigestion and sour stomach when accompanied by headache or body aches and pains
- upset stomach with headache from overindulgence in food or drink
- headache, body aches, and pain alone

Warnings

Reye's syndrome

Children and teenagers who have or are recovering from chicken pox or flu-like symptoms should not use this product. When using this product, if changes in behavior with nausea and vomiting occur, consult a doctor because these symptoms could be an early sign of Reye's syndrome, a rare but serious illness

Allergy alert

Aspirin may cause a severe allergic reaction which may include

- hives
- facial swelling
- asthma (wheezing)
- shock

Stomach bleeding warning

This product contains an NSAID, which may cause severe stomach bleeding. The chance is higher if you

- are age 60 or older
- have had stomach ulcers or bleeding problems
- take a blood thinning (anticoagulant) or steroid drug

Do not use if

- you have ever had an allergic reaction to any other pain reliever/fever reducer
- you are allergic to aspirin

Ask a doctor before use if

- stomach bleeding warning applies to you
- you have a history of stomach problems, such as heartburn
- you have high blood pressure, heart disease, liver cirrhosis, or kidney disease
- you are taking a diuretic

Ask a doctor or pharmacist before use if

- you are presently taking a prescription drug. Antacids may interact with certain prescription drugs.
- you have diabetes, gout or arthritis

Stop use and ask a doctor if

- an allergic reaction occurs. Seek medical help right away
- symptoms get worse or last more than 10 days
- redness or swelling is present
- ringing in the ears or loss of hearing occurs
- new symptoms occur
- you experience any of the following signs of stomach bleeding: feel faint, vomit blood, have bloody or black stools, have stomach pain that does not get better

PREGNANCY OR BREAST FEEDING

If pregnant or breast-feeding, ask a health professional before use. It is especially important not to use aspirin during the last 3 months of pregnancy unless definitely directed to do so by a doctor because it may cause problems in the unborn child or complications during delivery.

Keep out of reach of children. In case of overdose, get medical help or contact a Poison Control Center right away.

Directions

- completely dissolve two tablets in 4 ounces of water before taking

Adults and children 12 years and over | 2 tablets every 4 hours do not exceed 8 tablets in 24 hours
60 years and older | 2 tablets every 4 hours do not exceed 4 tablets in 24 hours

Other Information

- each tablet contains: sodium 540 mg
- protect from excessive heat
- in water, this tablet contains principally the antacid sodium citrate and the analgesic sodium acetylsalicylate

Inactive Ingredients

none

Questions or Comments?

call 1-800-632-2993 M-F 8AM – 4:30PM MST

Distributed By:
MAGELLAN
DISTRIBUTION SOLUTIONS
Medley, Florida 33178

PRINCIPAL DISPLAY PANEL - 36 Tablet Packet Carton

Compare to
Alka-Seltzer®

Vida
Mia

Effervescent

Pain
Relief

Aspirin (NSAID)* / Pain Reliever, Citric Acid /
Antacid, Sodium Bicardbonate / Antacid.
*nonsteroidal anti-inflammatory drug

Fast Relief of:
• Heartburn • Acid Indigestion
• Sour Stomach with Headache
• Body Aches and Pains

36
Tablets